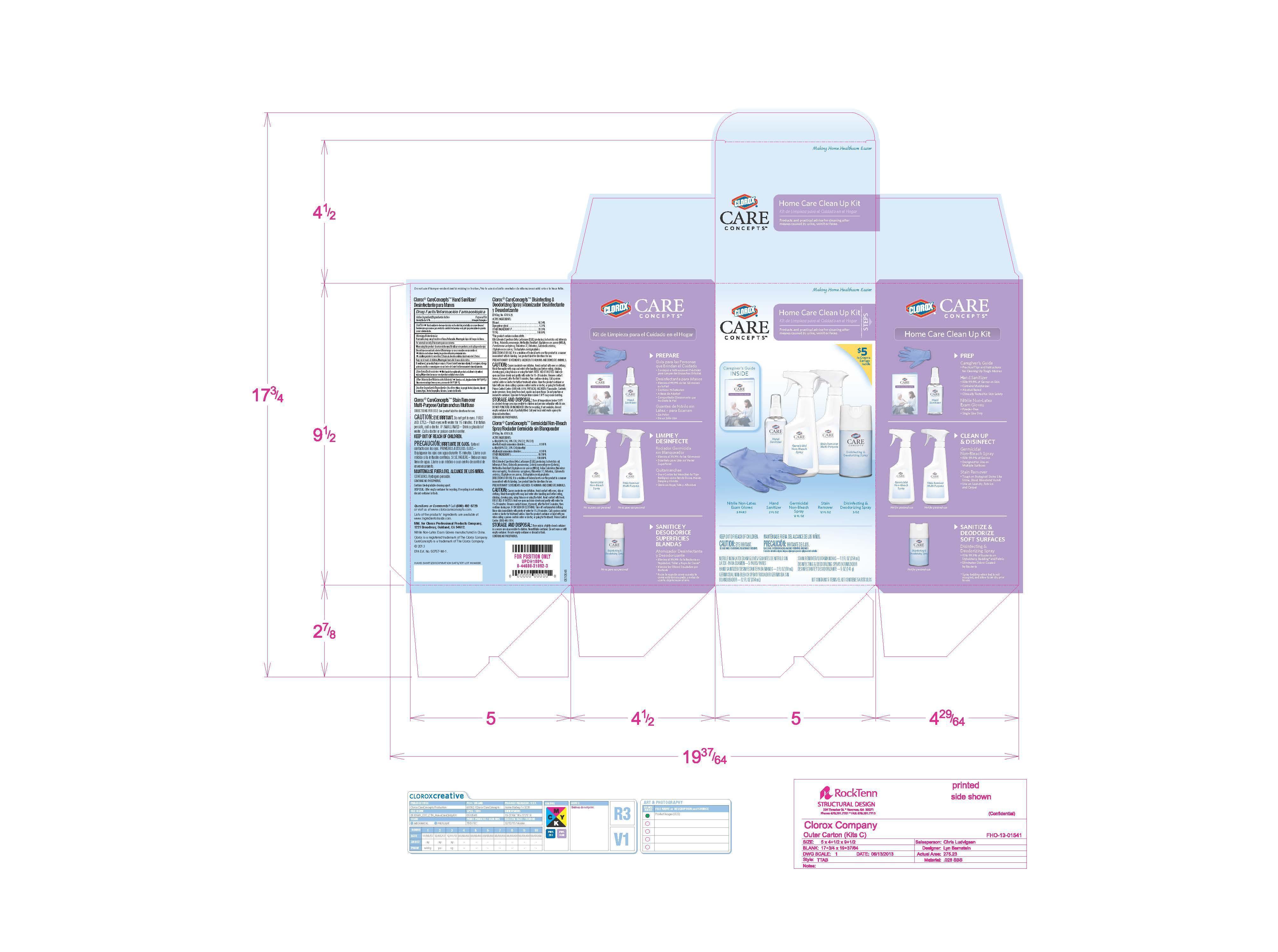 DRUG LABEL: Clorox Care Concepts
NDC: 26509-0005 | Form: KIT | Route: TOPICAL
Manufacturer: The Clorox Company
Category: otc | Type: HUMAN OTC DRUG LABEL
Date: 20140821

ACTIVE INGREDIENTS: ALCOHOL 67 mL/100 mL
INACTIVE INGREDIENTS: water; ISOPROPYL ALCOHOL; GLYCERIN; GLYCERYL LAURATE

Home Care Clean Up Kit

Active Ingredient

Alcohol 67%

Purpose

Antiseptic

Use

Hand sanitizer to decrease bacteria on the skin that potentially can cause disease

Warnings

Flammable. Keep away from fire or flame.
For external use only.

When using this product, do not use in the eyes.

Discontinue use and ask a doctor if

- irritate and redness develop.
- condition persists for more than 72 hours.

Keep out of reach of children.
If swallowed, get medical help or contact a Poison Control Center immediately.

Directions

Wet hands thoroughly with product and allow to dry without wiping.

Other Information

Store in a cool, dry place below 104 deg F (40 deg C).

Inactive Ingredients

Water, Isopropyl Alcohol, Glycerin, Glyceryl Laurate.

PACKAGE LABEL

Clorox Care Concepts

Home Care Clean Up Kit

Nitrile Non-Latex Exam Gloves

Hand Sanitizer